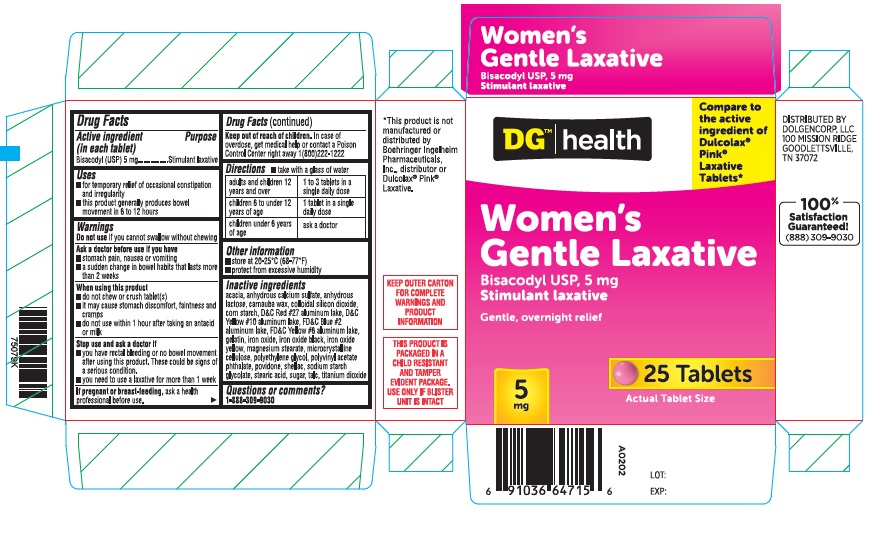 DRUG LABEL: Womens Laxative
NDC: 55910-848 | Form: TABLET, COATED
Manufacturer: Dolgencorp, Inc.
Category: otc | Type: HUMAN OTC DRUG LABEL
Date: 20211201

ACTIVE INGREDIENTS: BISACODYL 5 mg/1 1
INACTIVE INGREDIENTS: ACACIA; CALCIUM SULFATE ANHYDROUS; CARNAUBA WAX; SILICON DIOXIDE; STARCH, CORN; D&C RED NO. 27 ALUMINUM LAKE; FD&C BLUE NO. 2; FERRIC OXIDE RED; FERROSOFERRIC OXIDE; FERRIC OXIDE YELLOW; FD&C YELLOW NO. 6; MAGNESIUM STEARATE; CELLULOSE, MICROCRYSTALLINE; POLYETHYLENE GLYCOL 400; POVIDONE; SHELLAC; SODIUM STARCH GLYCOLATE TYPE A CORN; STEARIC ACID; SUCROSE; TALC; TITANIUM DIOXIDE; POLYVINYL ACETATE PHTHALATE; GELATIN; ANHYDROUS LACTOSE

Gentle Laxative

Active ingredient (in each tablet)

Bisacodyl USP 5 mg

Purpose

Stimulant laxative

Use

- for temporary relief of occasional constipation and irregularity
- this product generally produces a bowel movement in 6 to 12 hours

Warnings

Do not use

if you cannot swallow without chewing.

Ask a doctor before use if you have

- stomach pain, nausea or vomiting
- a sudden change in bowel habits that lasts more than 2 weeks

When using this product

- do not chew or crush tablet(s)
- do not use within 1 hour after taking an antacid or milk
- it may cause stomach discomfort, faintness and cramps

Stop use and ask a doctor if

- you have rectal bleeding or no bowel movement after using this product. These could be signs of a serious condition.
- you need to use a laxative for more than 1 week

If pregnant or breast-feeding,

ask a health professional before use.

Keep out of reach of children

In case of overdose, get medical help or contact a Poison Control Center right away.

Directions

- take with a glass of water

adults and children 12 years of age and over | take 1 to 3 tablets in a single daily dose
children 6 to under 12 years of age | take 1 tablet in a single daily dose
children under 6 years of age | ask a doctor

Other information

- each tablet contains: magnesium 5 mg
- store between 20-25ºC (68-77ºF)

Inactive ingredients

acacia, calcium sulfate anhydrous, anhydrous lactose, carnauba wax, colloidal silicon dioxide, corn starch, D&C red # 27 aluminum lake, FD&C blue #2 aluminum lake, FD&C yellow #6 aluminum lake, gelatin, iron oxide, iron oxide black, iron oxide yellow, magnesium stearate, microcrystalline cellulose, polyethylene glycol, polyvinyl acetate phthalate, povidone, shellac, sodium starch glycolate, stearic acid, sugar, talc, titanium dioxide

Questions or comments?

Call 1-888-309-9030

PRINCIPLA DISPLAY PANEL

Compare to active ingredient of Dulcolax® Pink® Laxative*

Women's Gentle Laxative Tablets

Bisacodyl 5 mg

Stimulant laxative

Gentle, Overnight relief

*This product is not manufactured or distributed by Boehringer Ingelheim Pharmaceuticals, Inc., distributor or Dulcolax® Pink® Laxative

TAMPER EVIDENT: DO NOT USE IF CARTON IS OPENED OR IF BLISTER UNIT IS TORN, BROKEN OR SHOWS ANY SIGNS OF TAMPERING.

KEEP OUTER CARTON FOR COMPLETE WARNINGS AND PRODUCT INFORMATION.